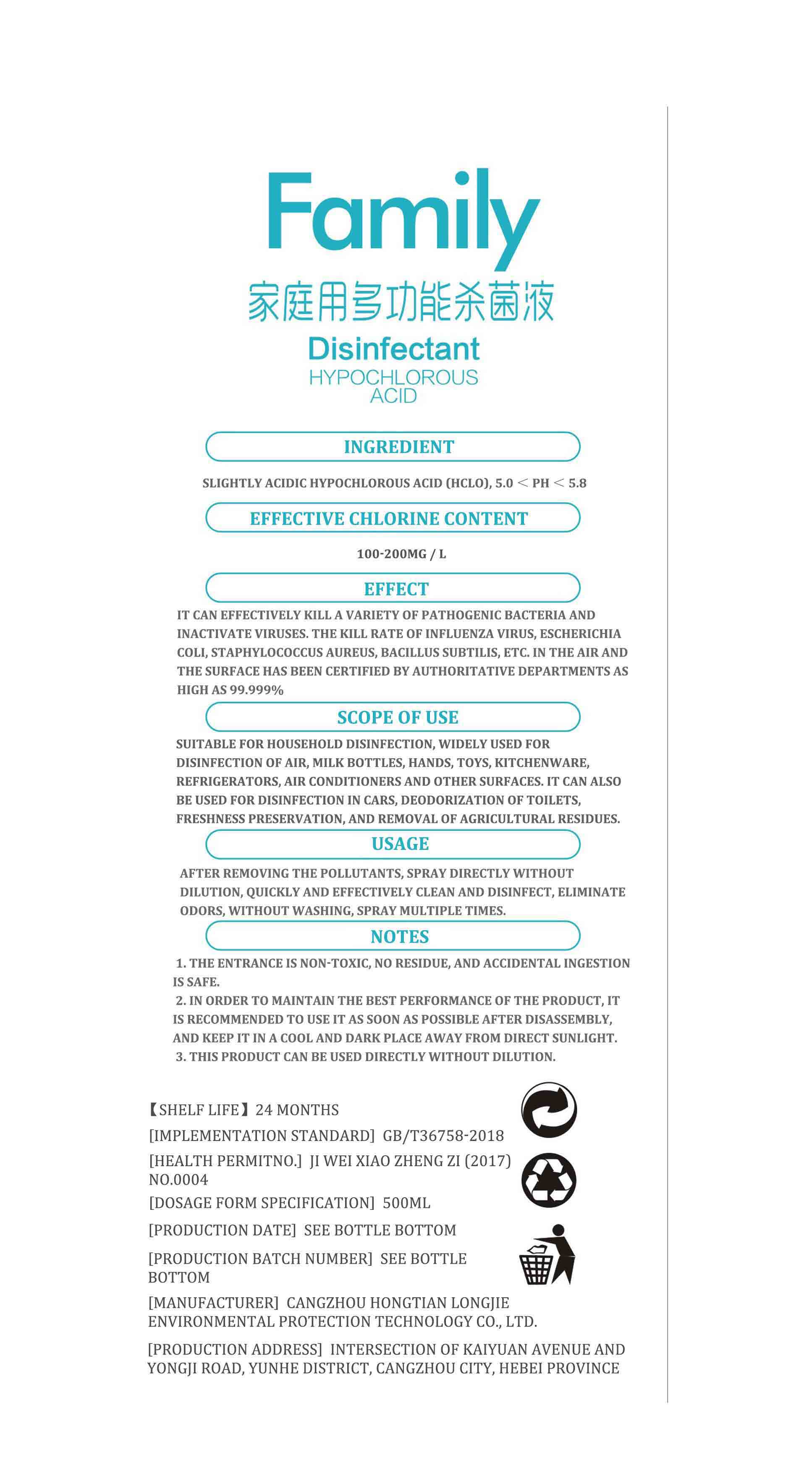 DRUG LABEL: Family Disinfectant
NDC: 77915-001 | Form: LIQUID
Manufacturer: Cangzhou HongtianLangjie Environmental Technology Co., Ltd.
Category: otc | Type: HUMAN OTC DRUG LABEL
Date: 20200528

ACTIVE INGREDIENTS: HYPOCHLOROUS ACID 20 mg/100 mL
INACTIVE INGREDIENTS: WATER

Family Disinfectant-hongtianlangjie

Active Ingredient(s)

Effective Chlorine 100-200mg/L

Purpose

Antiseptic, Disinfectant

Use

Suitable for household disinfection, widely used for disinfection of air, milk bottles, hands, toys, kitchenware, refrigerators, air conditioners and other surfaces. It can also be uesed for disinfection in cars, deodorization of toilets, freshness preservation, and removal of agricultural residues.

Warnings

For external use only. Flammable. Keep away from heat or flame

Do not use

- in children less than 2 months of age
- on open skin wounds

When using this product keep out of eyes, ears, and mouth. In case of contact with eyes, rinse eyes thoroughly with water.
Stop use and ask a doctor if irritation or rash occurs. These may be signs of a serious condition.
Keep out of reach of children. If swallowed, get medical help or contact a Poison Control Center right away.

Stop use and ask a doctor if irritation or rash occurs. These may be signs of a serious condition.

Keep out of reach of children. If swallowed, get medical help or contact a Poison Control Center right away.

Directions

- Place enough product on hands to cover all surfaces. Rub hands together until dry.
- Supervise children under 6 years of age when using this product to avoid swallowing.

Other information

- Store between 15-30C (59-86F)
- Avoid freezing and excessive heat above 40C (104F)

Inactive ingredients

Water, Sodium chloride, sodium carbonate

Package Label - Principal Display Panel

500 mL NDC: 77915-001-01